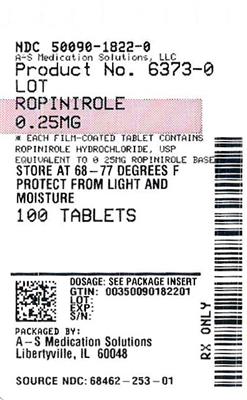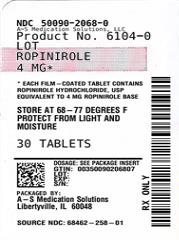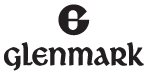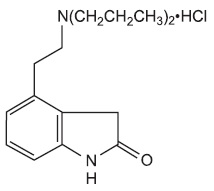 DRUG LABEL: ropinirole
NDC: 50090-1822 | Form: TABLET, FILM COATED
Manufacturer: A-S Medication Solutions
Category: prescription | Type: HUMAN PRESCRIPTION DRUG LABEL
Date: 20260206

ACTIVE INGREDIENTS: ROPINIROLE HYDROCHLORIDE 0.25 mg/1 1
INACTIVE INGREDIENTS: CITRIC ACID MONOHYDRATE; CROSCARMELLOSE SODIUM; ANHYDROUS LACTOSE; LACTOSE MONOHYDRATE; MAGNESIUM STEARATE; MICROCRYSTALLINE CELLULOSE; HYDROXYPROPYL METHYLCELLULOSE; POLYETHYLENE GLYCOL, UNSPECIFIED; TALC; TITANIUM DIOXIDE

HIGHLIGHTS OF PRESCRIBING INFORMATION

These highlights do not include all the information needed to use ROPINIROLE TABLETS safely and effectively. See full prescribing information for ROPINIROLE TABLETS.
ROPINIROLE tablets, for oral use
Initial U.S. Approval: 1997

1 INDICATIONS AND USAGE

Ropinirole tablets are a non-ergoline dopamine agonist indicated for the treatment of Parkinson’s disease (PD) and moderate-to-severe primary Restless Legs Syndrome (RLS). (1.1, 1.2)

2 DOSAGE AND ADMINISTRATION

- Ropinirole tablets can be taken with or without food. (2.1)
- Retitration of ropinirole tablets may be warranted if therapy is interrupted. (2.1)

Parkinson’s Disease:

- The recommended starting dose is 0.25 mg taken three times daily; titrate to a maximum daily dose of 24 mg. (2.2)
- Renal Impairment: The maximum recommended dose is 18 mg/day in patients with end-stage renal disease on hemodialysis. (2.2)

Restless Legs Syndrome:

- The recommended starting dose is 0.25 mg once daily, 1 to 3 hours before bedtime, titrate to a maximum recommended dose of 4 mg daily. (2.3)
- Renal Impairment: The maximum recommended dose is 3 mg/day in patients with end-stage renal disease on hemodialysis. (2.3)

3 DOSAGE FORMS AND STRENGTHS

Tablets: 0.25 mg, 0.5 mg, 1 mg, 2 mg, 3 mg, 4 mg, and 5 mg (3)

4 CONTRAINDICATIONS

History of hypersensitivity/allergic reaction (including urticaria, angioedema, rash, pruritus) to ropinirole or to any of the excipients. (4)

5 WARNINGS AND PRECAUTIONS

- Sudden onset of sleep and somnolence may occur (5.1)
- Syncope may occur (5.2)
- Hypotension, including orthostatic hypotension may occur (5.3)
- May cause hallucinations and psychotic-like behaviors (5.4)
- May cause or exacerbate dyskinesia (5.5)
- May cause problems with impulse control or compulsive behaviors (5.6)

6 ADVERSE REACTIONS

Most common adverse reactions (incidence with ropinirole at least 5% greater than placebo) in the respective indications were:

- Early PD: Nausea, somnolence, dizziness, syncope, asthenic condition, viral infection, leg edema, vomiting, and dyspepsia. (6.1)
- Advanced PD: Dyskinesia, somnolence, nausea, dizziness, confusion, hallucinations, sweating, and headache. (6.1)
- RLS: Nausea, vomiting, somnolence, dizziness, and asthenic condition. (6.1)

To report SUSPECTED ADVERSE REACTIONS, contact Glenmark Pharmaceuticals Inc., USA at 1 (888) 721-7115 or FDA at 1-800-FDA-1088 or www.fda.gov/medwatch.

7 DRUG INTERACTIONS

- Inhibitors or inducers of CYP1A2: May alter the clearance of ropinirole; dose adjustment of ropinirole may be required. (7.1, 12.3)
- Hormone replacement therapy (HRT): Starting or stopping HRT may require dose adjustment of ropinirole. (7.2, 12.3)
- Dopamine antagonists (e.g., neuroleptics, metoclopramide): May reduce efficacy of ropinirole. (7.3)

8 USE IN SPECIFIC POPULATIONS

Pregnancy: Based on animal data, may cause fetal harm. (8.1)

FULL PRESCRIBING INFORMATION

1 INDICATIONS AND USAGE

1.1 Parkinson's Disease

Ropinirole tablets are indicated for the treatment of Parkinson’s disease.

1.2 Restless Legs Syndrome

Ropinirole tablets are indicated for the treatment of moderate-to-severe primary Restless Legs Syndrome (RLS).

2 DOSAGE AND ADMINISTRATION

2.1 General Dosing Recommendations

Ropinirole tablets can be taken with or without food [see Clinical Pharmacology (12.3)].

If a significant interruption in therapy with ropinirole tablets has occurred, retitration of therapy may be warranted.

2.2 Dosing for Parkinson's Disease

The recommended starting dose of ropinirole tablets for Parkinson’s disease is 0.25 mg 3 times daily. Based on individual patient therapeutic response and tolerability, if necessary, the dose should then be titrated with weekly increments as described in Table 1. After Week 4, if necessary, the daily dose may be increased by 1.5 mg/day on a weekly basis up to a dose of 9 mg/day, and then by up to 3 mg/day weekly up to a maximum recommended total daily dose of 24 mg/day (8 mg 3 times daily). Doses greater than 24 mg/day have not been tested in clinical trials.

Table 1. Ascending-Dose Schedule of Ropinirole Tablets for Parkinson’s Disease
Week | Dosage | Total Daily Dose
1 | 0.25 mg 3 times daily | 0.75 mg
2 | 0.5 mg 3 times daily | 1.5 mg
3 | 0.75 mg 3 times daily | 2.25 mg
4 | 1 mg 3 times daily | 3 mg

Ropinirole tablets should be discontinued gradually over a 7-day period in patients with Parkinson’s disease [see Warnings and Precautions (5.8)]. The frequency of administration should be reduced from 3 times daily to twice daily for 4 days. For the remaining 3 days, the frequency should be reduced to once daily prior to complete withdrawal of ropinirole tablets.

Renal Impairment

No dose adjustment is necessary in patients with moderate renal impairment (creatinine clearance of 30 to 50 mL/min). The recommended initial dose of ropinirole for patients with end-stage renal disease on hemodialysis is 0.25 mg 3 times a day. Further dose escalations should be based on tolerability and need for efficacy. The recommended maximum total daily dose is 18 mg/day in patients receiving regular dialysis. Supplemental doses after dialysis are not required. The use of ropinirole tablets in patients with severe renal impairment without regular dialysis has not been studied.

2.3 Dosing for Restless Legs Syndrome

The recommended adult starting dose for RLS is 0.25 mg once daily 1 to 3 hours before bedtime. After 2 days, if necessary, the dose can be increased to 0.5 mg once daily, and to 1 mg once daily at the end of the first week of dosing, then as shown in Table 2 as needed to achieve efficacy. Titration should be based on individual patient therapeutic response and tolerability, up to a maximum recommended dose of 4 mg daily. For RLS, the safety and effectiveness of doses greater than 4 mg once daily have not been established.

Table 2. Dose Titration Schedule of Ropinirole Tablets for Restless Legs Syndrome
Day/Week | Dose to be taken once daily; 1 to 3 hours before bedtime
Days 1 and 2 | 0.25 mg
Days 3 to 7 | 0.5 mg
Week 2 | 1 mg
Week 3 | 1.5 mg
Week 4 | 2 mg
Week 5 | 2.5 mg
Week 6 | 3 mg
Week 7 | 4 mg

When discontinuing ropinirole tablets in patients with RLS, gradual reduction of the daily dose is recommended [see Warnings and Precautions (5.8, 5.9)].

Renal Impairment

No dose adjustment is necessary in patients with moderate renal impairment (creatinine clearance of 30 to 50 mL/min). The recommended initial dose of ropinirole for patients with end-stage renal disease on hemodialysis is 0.25 mg once daily. Further dose escalations should be based on tolerability and need for efficacy. The recommended maximum total daily dose is 3 mg/day in patients receiving regular dialysis. Supplemental doses after dialysis are not required. The use of ropinirole tablets in patients with severe renal impairment without regular dialysis has not been studied.

3 DOSAGE FORMS AND STRENGTHS

- 0.25 mg: white to off-white, circular, beveled edged, biconvex film-coated tablets with ‘2’ over ‘53’ debossed on one side and ‘G’ on the other side
- 0.5 mg: pale yellow to yellow, circular, beveled edged, biconvex film-coated tablets with ‘2’ over ‘54’ debossed on one side and ‘G’ on the other side
- 1 mg: pale green to green, circular, beveled edged, biconvex film-coated tablets with ‘2’ over ‘55’ debossed on one side and ‘G’ on the other side
- 2 mg: pale pink to pink, circular, beveled edged, biconvex film-coated tablets with ‘2’ over ‘56’ debossed on one side and ‘G’ on the other side
- 3 mg: purple, circular, beveled edged, biconvex film-coated tablets with ‘2’ over ‘57’ debossed on one side and ‘G’ on the other side
- 4 mg: pale brown to brown, circular, beveled edged, biconvex film-coated tablets with ‘2’ over ‘58’ debossed on one side and ‘G’ on the other side
- 5 mg: blue, circular, beveled edged, biconvex film-coated tablets with ‘2’ over ‘59’ debossed on one side and ‘G’ on the other side

4 CONTRAINDICATIONS

Ropinirole tablets are contraindicated in patients known to have a hypersensitivity/allergic reaction (including urticaria, angioedema, rash, pruritus) to ropinirole or to any of the excipients.

5 WARNINGS AND PRECAUTIONS

5.1 Falling Asleep during Activities of Daily Living and Somnolence

Patients treated with ropinirole have reported falling asleep while engaged in activities of daily living, including driving or operating machinery, which sometimes resulted in accidents. Although many of these patients reported somnolence while on ropinirole, some perceived that they had no warning signs, such as excessive drowsiness, and believed that they were alert immediately prior to the event. Some have reported these events more than 1 year after initiation of treatment.

In controlled clinical trials, somnolence was commonly reported in patients receiving ropinirole and was more frequent in Parkinson’s disease (up to 40% ropinirole, 6% placebo) than in RLS (12% ropinirole, 6% placebo) [see Adverse Reactions (6.1)].

It has been reported that falling asleep while engaged in activities of daily living usually occurs in a setting of pre-existing somnolence, although patients may not give such a history. For this reason, prescribers should reassess patients for drowsiness or sleepiness, especially since some of the events occur well after the start of treatment. Prescribers should also be aware that patients may not acknowledge drowsiness or sleepiness until directly questioned about drowsiness or sleepiness during specific activities.

Before initiating treatment with ropinirole, patients should be advised of the potential to develop drowsiness and specifically asked about factors that may increase the risk with ropinirole such as concomitant sedating medications or alcohol, the presence of sleep disorders (other than RLS), and concomitant medications that increase ropinirole plasma levels (e.g., ciprofloxacin) [see Drug Interactions (7.1)]. If a patient develops significant daytime sleepiness or episodes of falling asleep during activities that require active participation (e.g., driving a motor vehicle, conversations, eating), ropinirole should ordinarily be discontinued [see Dosage and Administration (2.2, 2.3)]. If a decision is made to continue ropinirole, patients should be advised to not drive and to avoid other potentially dangerous activities. There is insufficient information to establish that dose reduction will eliminate episodes of falling asleep while engaged in activities of daily living.

5.2 Syncope

Syncope, sometimes associated with bradycardia, was observed in association with treatment with ropinirole in both patients with Parkinson’s disease and patients with RLS. In controlled clinical trials in patients with Parkinson’s disease, syncope was observed more frequently in patients receiving ropinirole than in patients receiving placebo (early Parkinson’s disease without levodopa [L-dopa]: ropinirole 12%, placebo 1%; advanced Parkinson’s disease: ropinirole 3%, placebo 2%). Syncope was reported in 1% of patients treated with ropinirole for RLS in 12-week, placebo-controlled clinical trials compared with 0.2% of patients treated with placebo [see Adverse Reactions (6.1)]. Most cases occurred more than 4 weeks after initiation of therapy with ropinirole and were usually associated with a recent increase in dose.

Because the trials conducted with ropinirole excluded patients with significant cardiovascular disease, patients with significant cardiovascular disease should be treated with caution.

Approximately 4% of patients with Parkinson’s disease enrolled in Phase 1 trials had syncope following a 1-mg dose of ropinirole. In 2 trials in patients with RLS that used a forced-titration regimen and orthostatic challenge with intensive blood pressure monitoring, 2% of RLS patients treated with ropinirole compared with 0% of patients receiving placebo reported syncope.

In Phase 1 trials including healthy volunteers, the incidence of syncope was 2%. Of note, 1 subject with syncope developed hypotension, bradycardia, and sinus arrest; the subject recovered spontaneously without intervention.

5.3 Hypotension/Orthostatic Hypotension

Patients with Parkinson’s disease may have impaired ability to respond normally to a fall in blood pressure after standing from lying down or seated position. Patients on ropinirole should be monitored for signs and symptoms of orthostatic hypotension, especially during dose escalation, and should be informed of the risk for syncope and hypotension [see Patient Counseling Information (17)].

Although the clinical trials were not designed to systematically monitor blood pressure, there were individual reported cases of orthostatic hypotension in early Parkinson’s disease (without L-dopa) in patients treated with ropinirole. Most of these cases occurred more than 4 weeks after initiation of therapy with ropinirole and were usually associated with a recent increase in dose.

In 12-week, placebo-controlled trials of patients with RLS, the adverse event orthostatic hypotension was reported by 4 of 496 patients (0.8%) treated with ropinirole compared with 2 of 500 patients (0.4%) receiving placebo.

In 2 Phase 2 trials in patients with RLS, 14 of 55 patients (25%) receiving ropinirole experienced an adverse event of hypotension or orthostatic hypotension compared with none of the 27 patients receiving placebo. In these trials, 11 of the 55 patients (20%) receiving ropinirole and 3 of the 26 patients (12%) who had post-dose blood pressure assessments following placebo experienced an orthostatic blood pressure decrease of at least 40 mm Hg systolic and/or at least 20 mm Hg diastolic.

In Phase 1 trials of ropinirole with healthy volunteers who received single doses on more than one occasion without titration, 7% had documented symptomatic orthostatic hypotension. These episodes appeared mainly at doses above 0.8 mg, and these doses are higher than the starting doses recommended for patients with either Parkinson’s disease or with RLS. In most of these individuals, the hypotension was accompanied by bradycardia but did not develop into syncope [see Warnings and Precautions (5.2)].

Although dizziness is not a specific manifestation of hypotension or orthostatic hypotension, patients with hypotension or orthostatic hypotension frequently reported dizziness. In controlled clinical trials, dizziness was a common adverse reaction in patients receiving ropinirole and was more frequent in patients with Parkinson’s disease or with RLS receiving ropinirole than in patients receiving placebo (early Parkinson’s disease without L-dopa: Ropinirole 40%, placebo 22%; advanced Parkinson’s disease: Ropinirole 26%, placebo 16%; RLS: Ropinirole 11%, placebo 5%). Dizziness of sufficient severity to cause trial discontinuation of ropinirole was 4% in patients with early Parkinson’s disease without L-dopa, 3% in patients with advanced Parkinson’s disease, and 1% in patients with RLS [see Adverse Reactions (6.1)].

5.4 Hallucinations/Psychotic-Like Behavior

In double-blind, placebo-controlled, early-therapy trials in patients with Parkinson’s disease who were not treated with L-dopa, 5.2% (8 of 157) of patients treated with ropinirole reported hallucinations, compared with 1.4% of patients on placebo (2 of 147). Among those patients receiving both ropinirole and L-dopa in advanced Parkinson’s disease trials, 10.1% (21 of 208) were reported to experience hallucinations, compared with 4.2% (5 of 120) of patients treated with placebo and L-dopa.

The incidence of hallucination was increased in elderly patients (i.e., older than 65 years) treated with extended-release ropinirole [see Use in Specific Populations (8.5)].

Postmarketing reports indicate that patients with Parkinson’s disease or RLS may experience new or worsening mental status and behavioral changes, which may be severe, including psychotic-like behavior during treatment with ropinirole or after starting or increasing the dose of ropinirole. Other drugs prescribed to improve the symptoms of Parkinson’s disease or RLS can have similar effects on thinking and behavior. This abnormal thinking and behavior can consist of one or more of a variety of manifestations including paranoid ideation, delusions, hallucinations, confusion, psychotic-like behavior, symptoms of mania (e.g., insomnia, psychomotor agitation), disorientation, aggressive behavior, agitation, and delirium.

Patients with a major psychotic disorder should ordinarily not be treated with ropinirole because of the risk of exacerbating the psychosis. In addition, certain medications used to treat psychosis may exacerbate the symptoms of Parkinson’s disease and may decrease the effectiveness of ropinirole [see Drug Interactions (7.3)].

5.5 Dyskinesia

Ropinirole may cause or exacerbate pre-existing dyskinesia in patients treated with L-dopa for Parkinson’s disease.

In double-blind, placebo-controlled trials in advanced Parkinson’s disease, dyskinesia was much more common in patients treated with ropinirole than in those treated with placebo. Among those patients receiving both ropinirole and L-dopa in advanced Parkinson’s disease trials, 34% were reported to experience dyskinesia, compared with 13% of patients treated with placebo [see Adverse Reactions (6.1)].

Decreasing the dose of dopaminergic medications may ameliorate this adverse reaction.

5.6 Impulse Control/Compulsive Behaviors

Reports suggest that patients can experience intense urges to gamble, increased sexual urges, intense urges to spend money, binge or compulsive eating, and/or other intense urges, and the inability to control these urges while taking one or more of the medications, including ropinirole, that increase central dopaminergic tone. In some cases, although not all, these urges were reported to have stopped when the dose was reduced or the medication was discontinued. Because patients may not recognize these behaviors as abnormal, it is important for prescribers to specifically ask patients or their caregivers about the development of new or increased gambling urges, sexual urges, uncontrolled spending, binge or compulsive eating, or other urges while being treated with ropinirole for Parkinson’s disease or RLS. Physicians should consider dose reduction or stopping the medication if a patient develops such urges while taking ropinirole.

5.7 Withdrawal-Emergent Hyperpyrexia and Confusion

A symptom complex resembling the neuroleptic malignant syndrome (characterized by elevated temperature, muscular rigidity, altered consciousness, and autonomic instability), with no other obvious etiology, has been reported in association with rapid dose reduction of, withdrawal of, or changes in, dopaminergic therapy. Therefore, it is recommended that the dose be tapered at the end of treatment with ropinirole as a prophylactic measure [see Dosage and Administration (2.2, 2.3)].

5.8 Withdrawal Symptoms

Symptoms including insomnia, apathy, anxiety, depression, fatigue, sweating, and pain have been reported during taper or after discontinuation of dopamine agonists, including ropinirole. These symptoms generally do not respond to levodopa.

Prior to discontinuation of ropinirole, patients should be informed about potential withdrawal symptoms, and monitored during and after discontinuation. In case of severe withdrawal symptoms, a trial re-administration of a dopamine agonist at the lowest effective dose may be considered.

5.9 Augmentation and Early-Morning Rebound in Restless Legs Syndrome

Augmentation is a phenomenon in which dopaminergic medication causes a worsening of symptom severity above and beyond the level at the time the medication was started. The symptoms of augmentation may include the earlier onset of symptoms in the evening (or even the afternoon), increase in symptoms, and spread of symptoms to involve other extremities. Augmentation has been described during therapy for RLS. Rebound refers to new onset of symptoms in the early morning hours. Augmentation and/or early-morning rebound have been observed in a postmarketing trial of ropinirole. If augmentation or early-morning rebound occurs, the use of ropinirole should be reviewed and dosage adjustment or discontinuation of treatment should be considered. When discontinuing ropinirole in patients with RLS, gradual reduction of the daily dose is recommended whenever possible [see Dosage and Administration (2.3)].

5.10 Fibrotic Complications

Cases of retroperitoneal fibrosis, pulmonary infiltrates, pleural effusion, pleural thickening, pericarditis, and cardiac valvulopathy have been reported in some patients treated with ergot-derived dopaminergic agents. While these complications may resolve when the drug is discontinued, complete resolution does not always occur.

Although these adverse reactions are believed to be related to the ergoline structure of these compounds, whether other, non-ergot-derived dopamine agonists, such as ropinirole, can cause them is unknown.

Cases of possible fibrotic complications, including pleural effusion, pleural fibrosis, interstitial lung disease, and cardiac valvulopathy have been reported in the development program and postmarketing experience for ropinirole. While the evidence is not sufficient to establish a causal relationship between ropinirole and these fibrotic complications, a contribution of ropinirole cannot be excluded.

5.11 Retinal Pathology

Retinal degeneration was observed in albino rats in the 2-year carcinogenicity study at all doses tested. The lowest dose tested (1.5 mg/kg/day) is less than the maximum recommended human dose (MRHD) for Parkinson’s disease (24 mg/day) on a mg/m^2 basis. Retinal degeneration was not observed in a 3-month study in pigmented rats, in a 2-year carcinogenicity study in albino mice, or in 1-year studies in monkeys or albino rats. The significance of this effect for humans has not been established, but involves disruption of a mechanism that is universally present in vertebrates (e.g., disk shedding).

Ocular electroretinogram assessments were conducted during a 2-year, double-blind, multicenter, flexible dose, L-dopa-controlled clinical trial of ropinirole in patients with Parkinson’s disease; 156 patients (78 on ropinirole, mean dose: 11.9 mg/day, and 78 on L-dopa, mean dose: 555.2 mg/day) were evaluated for evidence of retinal dysfunction through electroretinograms. There was no clinically meaningful difference between the treatment groups in retinal function over the duration of the trial.

5.12 Binding to Melanin

Ropinirole binds to melanin-containing tissues (e.g., eyes, skin) in pigmented rats. After a single dose, long-term retention of drug was demonstrated, with a half-life in the eye of 20 days.

6 ADVERSE REACTIONS

The following adverse reactions are described in more detail in other sections of the label:

- Hypersensitivity [see Contraindications (4)]
- Falling asleep during activities of daily living and somnolence [see Warnings and Precautions (5.1)]
- Syncope [see Warnings and Precautions (5.2)]
- Hypotension/orthostatic hypotension [see Warnings and Precautions (5.3)]
- Hallucinations/psychotic-like behavior [see Warnings and Precautions (5.4)]
- Dyskinesia [see Warnings and Precautions (5.5)]
- Impulse control/compulsive behaviors [see Warnings and Precautions (5.6)]
- Withdrawal-emergent hyperpyrexia and confusion [see Warnings and Precautions (5.7)]
- Withdrawal Symptoms [see Warnings and Precautions (5.8)]
- Augmentation and early-morning rebound in RLS [see Warnings and Precautions (5.9)]
- Fibrotic complications [see Warnings and Precautions (5.10)]
- Retinal pathology [see Warnings and Precautions (5.11)]

6.1 Clinical Trials Experience

Because clinical trials are conducted under widely varying conditions, adverse reaction rates observed in the clinical trials of a drug cannot be directly compared with rates in the clinical trials of another drug (or of another development program of a different formulation of the same drug) and may not reflect the rates observed in practice.

Parkinson's Disease

During the premarketing development of ropinirole, patients received ropinirole either without L-dopa (early Parkinson’s disease trials) or as concomitant therapy with L-dopa (advanced Parkinson’s disease trials). Because these 2 populations may have differential risks for various adverse reactions, this section will in general present adverse reaction data for these 2 populations separately.

Early Parkinson’s Disease (without L-dopa):

In the double-blind, placebo-controlled trials in patients with early-stage Parkinson’s disease, the most commonly observed adverse reactions in patients treated with ropinirole (incidence at least 5% greater than placebo) were nausea, somnolence, dizziness, syncope, asthenic condition (i.e., asthenia, fatigue, and/or malaise), viral infection, leg edema, vomiting, and dyspepsia.

Approximately 24% of patients treated with ropinirole who participated in the double-blind, placebo-controlled early Parkinson’s disease (without L-dopa) trials discontinued treatment due to adverse reactions compared with 13% of patients who received placebo. The most common adverse reactions in patients treated with ropinirole (incidence at least 2% greater than placebo) of sufficient severity to cause discontinuation were nausea and dizziness.

Table 3 lists treatment-emergent adverse reactions that occurred in at least 2% of patients with early Parkinson’s disease (without L-dopa) treated with ropinirole participating in the double-blind, placebo-controlled trials and were numerically more common than the incidence for placebo-treated patients. In these trials, either ropinirole or placebo was used as early therapy (i.e., without L-dopa).

Table 3. Treatment-Emergent Adverse Reaction Incidence in Double-blind, Placebo-Controlled Early Parkinson’s Disease (without L-dopa) Trials (Events ≥2% of Patients Treated with Ropinirole and Numerically More Frequent than the Placebo Group)a

Body System/Adverse Reaction | Ropinirole; (n = 157); (%) | Placebo; (n = 147); (%)
Autonomic nervous system
Flushing | 3 | 1
Dry mouth | 5 | 3
Increased sweating | 6 | 4
Body as a whole
Asthenic conditionb | 16 | 5
Chest pain | 4 | 2
Dependent edema | 6 | 3
Leg edema | 7 | 1
Pain | 8 | 4
Cardiovascular general
Hypertension | 5 | 3
Hypotension | 2 | 0
Orthostatic symptoms | 6 | 5
Syncope | 12 | 1
Central/peripheral nervous system
Dizziness | 40 | 22
Hyperkinesia | 2 | 1
Hypesthesia | 4 | 2
Vertigo | 2 | 0
Gastrointestinal
Abdominal pain | 6 | 3
Anorexia | 4 | 1
Dyspepsia | 10 | 5
Flatulence | 3 | 1
Nausea | 60 | 22
Vomiting | 12 | 7
Heart rate/rhythm
Extrasystoles | 2 | 1
Atrial fibrillation | 2 | 0
Palpitation | 3 | 2
Tachycardia | 2 | 0
Metabolic/nutritional
Increased alkaline phosphatase | 3 | 1
Psychiatric
Amnesia | 3 | 1
Impaired concentration | 2 | 0
Confusion | 5 | 1
Hallucination | 5 | 1
Somnolence | 40 | 6
Yawning | 3 | 0
Reproductive male
Impotence | 3 | 1
Resistance mechanism
Viral infection | 11 | 3
Respiratory
Bronchitis | 3 | 1
Dyspnea | 3 | 0
Pharyngitis | 6 | 4
Rhinitis | 4 | 3
Sinusitis | 4 | 3
Urinary
Urinary tract infection | 5 | 4
Vascular extracardiac
Peripheral ischemia | 3 | 0
Vision
Eye abnormality | 3 | 1
Abnormal vision | 6 | 3
Xerophthalmia | 2 | 0

a Patients may have reported multiple adverse reactions during the trial or at discontinuation; thus, patients may be included in more than one category.
b Asthenic condition (i.e., asthenia, fatigue, and/or malaise).

Advanced Parkinson’s Disease (with L-dopa):

In the double-blind, placebo-controlled trials in patients with advanced-stage Parkinson’s disease, the most commonly observed adverse reactions in patients treated with ropinirole (incidence at least 5% greater than placebo) were dyskinesia, somnolence, nausea, dizziness, confusion, hallucinations, increased sweating, and headache.

Approximately 24% of patients who received ropinirole in the double-blind, placebo-controlled advanced Parkinson’s disease (with L-dopa) trials discontinued treatment due to adverse reactions compared with 18% of patients who received placebo. The most common adverse reaction in patients treated with ropinirole (incidence at least 2% greater than placebo) of sufficient severity to cause discontinuation was dizziness.

Table 4 lists treatment-emergent adverse reactions that occurred in at least 2% of patients with advanced Parkinson’s disease (with L-dopa) treated with ropinirole who participated in the double-blind, placebo-controlled trials and were numerically more common than the incidence for placebo-treated patients. In these trials, either ropinirole or placebo was used as an adjunct to L-dopa.

Table 4. Treatment-Emergent Adverse Reaction Incidence in Double-blind, Placebo-Controlled Advanced Parkinson’s Disease (with L-dopa) Trials (Events ≥2% of Patients Treated with Ropinirole and Numerically More Frequent than the Placebo Group)a

Body System/Adverse Reaction | Ropinirole; (n = 208); (%) | Placebo; (n = 120); (%)
Autonomic nervous system
Dry mouth | 5 | 1
Increased sweating | 7 | 2
Body as a whole
Increased drug level | 7 | 3
Pain | 5 | 3
Cardiovascular general
Hypotension | 2 | 1
Syncope | 3 | 2
Central/peripheral nervous system
Dizziness | 26 | 16
Dyskinesia | 34 | 13
Falls | 10 | 7
Headache | 17 | 12
Hypokinesia | 5 | 4
Paresis | 3 | 0
Paresthesia | 5 | 3
Tremor | 6 | 3
Gastrointestinal
Abdominal pain | 9 | 8
Constipation | 6 | 3
Diarrhea | 5 | 3
Dysphagia | 2 | 1
Flatulence | 2 | 1
Nausea | 30 | 18
Increased saliva | 2 | 1
Vomiting | 7 | 4
Metabolic/nutritional
Weight decrease | 2 | 1
Musculoskeletal
Arthralgia | 7 | 5
Arthritis | 3 | 1
Psychiatric
Amnesia | 5 | 1
Anxiety | 6 | 3
Confusion | 9 | 2
Abnormal dreaming | 3 | 2
Hallucination | 10 | 4
Nervousness | 5 | 3
Somnolence | 20 | 8
Red blood cell
Anemia | 2 | 0
Resistance mechanism
Upper respiratory tract infection | 9 | 8
Respiratory
Dyspnea | 3 | 2
Urinary
Pyuria | 2 | 1
Urinary incontinence | 2 | 1
Urinary tract infection | 6 | 3
Vision
Diplopia | 2 | 1

a Patients may have reported multiple adverse reactions during the trial or at discontinuation; thus, patients may be included in more than one category.

Restless Legs Syndrome

In the double-blind, placebo-controlled trials in patients with RLS, the most commonly observed adverse reactions in patients treated with ropinirole (incidence at least 5% greater than placebo) were nausea, vomiting, somnolence, dizziness, and asthenic condition (i.e., asthenia, fatigue, and/or malaise).

Approximately 5% of patients treated with ropinirole who participated in the double-blind, placebo-controlled trials in the treatment of RLS discontinued treatment due to adverse reactions compared with 4% of patients who received placebo. The most common adverse reaction in patients treated with ropinirole (incidence at least 2% greater than placebo) of sufficient severity to cause discontinuation was nausea.

Table 5 lists treatment-emergent adverse reactions that occurred in at least 2% of patients with RLS treated with ropinirole participating in the 12-week, double-blind, placebo-controlled trials and were numerically more common than the incidence for placebo-treated patients.

Table 5. Treatment-Emergent Adverse Reaction Incidence in Double-blind, Placebo-Controlled Restless Legs Syndrome Trials (Events ≥2% of Patients Treated with Ropinirole and Numerically More Frequent than the Placebo Group)a

Body System/Adverse Reaction | Ropinirole; (n = 496); (%) | Placebo; (n = 500); (%)
Ear and labyrinth
Vertigo | 2 | 1
Gastrointestinal
Nausea | 40 | 8
Vomiting | 11 | 2
Diarrhea | 5 | 3
Dyspepsia | 4 | 3
Dry mouth | 3 | 2
Abdominal pain upper | 3 | 1
General disorders and administration site conditions
Asthenic conditionb | 9 | 4
Edema peripheral | 2 | 1
Infections and infestations
Nasopharyngitis | 9 | 8
Influenza | 3 | 2
Musculoskeletal and connective tissue
Arthralgia | 4 | 3
Muscle cramps | 3 | 2
Pain in extremity | 3 | 2
Nervous system
Somnolence | 12 | 6
Dizziness | 11 | 5
Paresthesia | 3 | 1
Respiratory, thoracic, and mediastinal
Cough | 3 | 2
Nasal congestion | 2 | 1
Skin and subcutaneous tissue
Hyperhidrosis | 3 | 1

a Patients may have reported multiple adverse reactions during the trial or at discontinuation; thus, patients may be included in more than one category.

b Asthenic condition (i.e., asthenia, fatigue, and/or malaise).

6.2 Postmarketing Experience

The following adverse reactions have been identified during postapproval use of ropinirole. Because these reactions are reported voluntarily from a population of uncertain size, it is not always possible to reliably estimate their frequency or establish a causal relationship to drug exposure.

General Disorders and Administration Site Conditions

Withdrawal symptoms [see Warnings and Precautions (5.8)]

7 DRUG INTERACTIONS

7.1 Cytochrome P450 1A2 Inhibitors and Inducers

In vitro metabolism studies showed that cytochrome P450 1A2 (CYP1A2) is the major enzyme responsible for the metabolism of ropinirole. There is thus the potential for inducers or inhibitors of this enzyme to alter the clearance of ropinirole. Therefore, if therapy with a drug known to be a potent inducer or inhibitor of CYP1A2 is stopped or started during treatment with ropinirole, adjustment of the dose of ropinirole may be required. Coadministration of ciprofloxacin, an inhibitor of CYP1A2, increases the AUC and Cmax of ropinirole [see Clinical Pharmacology (12.3)]. Cigarette smoking is expected to increase the clearance of ropinirole since CYP1A2 is known to be induced by smoking hormone replacement therapy [see Clinical Pharmacology (12.3)].

7.2 Estrogens

Population pharmacokinetic analysis revealed that higher doses of estrogens (usually associated with hormone replacement therapy) reduced the clearance of ropinirole. Starting or stopping may require adjustment of dosage of ropinirole [see Clinical Pharmacology (12.3)].

7.3 Dopamine Antagonists

Because ropinirole is a dopamine agonist, it is possible that dopamine antagonists such as neuroleptics (e.g., phenothiazines, butyrophenones, thioxanthenes) or metoclopramide may reduce the efficacy of ropinirole.

8 USE IN SPECIFIC POPULATIONS

8.1 Pregnancy

Risk Summary

There are no adequate data on the developmental risk associated with the use of ropinirole in pregnant women. In animal studies, ropinirole had adverse effects on development when administered to pregnant rats at doses similar to (neurobehavioral impairment) or greater than (teratogenicity and embryolethality at >36 times) the MRHD for Parkinson’s disease. Ropinirole doses associated with teratogenicity and embryolethality in pregnant rats were associated with maternal toxicity. In pregnant rabbits, ropinirole potentiated the teratogenic effects of L-dopa when these drugs were administered in combination [see Data].

In the U.S. general population, the estimated background risk of major birth defects and of miscarriage in clinically recognized pregnancies is 2% to 4% and 15% to 20%, respectively. The background risk of major birth defects and miscarriage in the indicated populations is unknown.

Data

Animal Data: Oral administration of ropinirole (0, 20, 60, 90, 120, or 150 mg/kg/day) to pregnant rats during organogenesis resulted in embryolethality, increased incidence of fetal malformations (digit, cardiovascular, and neural tube defects) and variations, and decreased fetal weight at the 2 highest doses. These doses were also associated with maternal toxicity. The highest no-effect dose for adverse effects on embryofetal development (90 mg/kg/day) is approximately 36 times the MRHD for Parkinson’s disease (24 mg/day) on a body surface area (mg/m^2) basis.

No effect on embryofetal development was observed in rabbits when ropinirole was administered alone during organogenesis at oral doses of 0, 1, 5, or 20 mg/kg/day (up to 16 times the MRHD on a mg/m^2 basis). In pregnant rabbits, there was a greater incidence and severity of fetal malformations (primarily digit defects) when ropinirole (10 mg/kg/day) was administered orally during gestation in combination with L-dopa (250 mg/kg/day) than when L-dopa was administered alone. This drug combination was also associated with maternal toxicity.

Oral administration of ropinirole (0, 0.1, 1, or 10 mg/kg/day) to rats during late gestation and continuing throughout lactation resulted in neurobehavioral impairment (decreased startle response) and decreased body weight in offspring at the highest dose. The no-effect dose of 1 mg/kg/day is less than the MRHD on a mg/m^2 basis.

8.2 Lactation

Risk Summary

There are no data on the presence of ropinirole in human milk, the effects of ropinirole on the breastfed infant, or the effects of ropinirole on milk production. However, inhibition of lactation is expected because ropinirole inhibits secretion of prolactin in humans. Ropinirole or metabolites, or both, are present in rat milk.

The developmental and health benefits of breastfeeding should be considered along with the mother’s clinical need for ropinirole and any potential adverse effects on the breastfed infant from ropinirole or from the underlying maternal condition.

8.4 Pediatric Use

Safety and effectiveness in pediatric patients have not been established.

8.5 Geriatric Use

Dose adjustment is not necessary in elderly (65 years and older) patients, as the dose of ropinirole is individually titrated to clinical therapeutic response and tolerability. Pharmacokinetic trials conducted in patients demonstrated that oral clearance of ropinirole is reduced by 15% in patients older than 65 years compared with younger patients [see Clinical Pharmacology (12.3)].

In flexible-dose clinical trials of extended-release ropinirole for Parkinson’s disease, 387 patients were 65 years and older and 107 patients were 75 years and older. Among patients receiving extended-release ropinirole, hallucination was more common in elderly patients (10%) compared with non-elderly patients (2%). In these trials, the incidence of overall adverse reactions increased with increasing age for both patients receiving extended-release ropinirole and placebo.

In the fixed-dose clinical trials of extended-release ropinirole, 176 patients were 65 years and older and 73 were 75 and older. Among patients with advanced Parkinson’s disease receiving extended-release ropinirole, vomiting and nausea were more common in patients greater than 65 years (5% and 9%, respectively) compared with patients less than 65 (1% and 7%, respectively).

8.6 Renal Impairment

No dose adjustment is necessary in patients with moderate renal impairment (creatinine clearance of 30 to 50 mL/min). For patients with end-stage renal disease on hemodialysis, a reduced maximum dose is recommended [see Dosage and Administration (2.2, 2.3), Clinical Pharmacology (12.3)].

The use of ropinirole in patients with severe renal impairment (creatinine clearance <30 mL/min) without regular dialysis has not been studied.

8.7 Hepatic Impairment

The pharmacokinetics of ropinirole have not been studied in patients with hepatic impairment.

10 OVERDOSAGE

The symptoms of overdose with ropinirole are related to its dopaminergic activity. General supportive measures are recommended. Vital signs should be maintained, if necessary.

In clinical trials, there have been patients who accidentally or intentionally took more than their prescribed dose of ropinirole. The largest overdose reported with ropinirole in clinical trials was 435 mg taken over a 7-day period (62.1 mg/day). Of patients who received a dose greater than 24 mg/day, reported symptoms included adverse events commonly reported during dopaminergic therapy (nausea, dizziness), as well as visual hallucinations, hyperhidrosis, claustrophobia, chorea, palpitations, asthenia, and nightmares. Additional symptoms reported in cases of overdose included vomiting, increased coughing, fatigue, syncope, vasovagal syncope, dyskinesia, agitation, chest pain, orthostatic hypotension, somnolence, and confusional state.

11 DESCRIPTION

Ropinirole Tablets, USP contain ropinirole, a non-ergoline dopamine agonist, as the hydrochloride salt. The chemical name of ropinirole hydrochloride, USP is 4-[2-(dipropylamino)ethyl]-1,3-dihydro-2H-indol-2-one and the empirical formula is C16H24N2O•HCl. The molecular weight is 296.84 g/mol (260.38 as the free base).

The structural formula is:

Ropinirole hydrochloride, USP is a pale cream to yellow powder with a melting range of 243°C to 250°C and a solubility of 133 mg/mL in water.

Each circular, beveled edged, biconvex film-coated tablet contains ropinirole hydrochloride, USP equivalent to ropinirole, 0.25 mg, 0.5 mg, 1 mg, 2 mg, 3 mg, 4 mg, or 5 mg. Inactive ingredients consist of citric acid anhydrous powder, croscarmellose sodium, lactose anhydrous, lactose monohydrate, magnesium stearate, and microcrystalline cellulose. The ingredients of the film coating for each tablet are as follows:

0.25 mg: Hypromellose, polyethylene glycol, talc and titanium dioxide.

0.5 mg: FD&C Blue no. 2 aluminum lake, ferric oxide red, ferric oxide yellow, hypromellose, polyethylene glycol, talc and titanium dioxide.

1 mg: FD&C Blue no. 2 aluminum lake, ferric oxide black, ferric oxide yellow, hypromellose, polyethylene glycol, talc and titanium dioxide.

2 mg: Ferric oxide red, hypromellose, polyethylene glycol, talc and titanium dioxide.

3 mg: Carmine, FD&C Blue no. 2 aluminum lake, FD&C Yellow no. 6 aluminum lake, hypromellose, polyethylene glycol, talc and titanium dioxide.

4 mg: Ferric oxide black, ferric oxide red, ferric oxide yellow, hypromellose, polyethylene glycol, talc and titanium dioxide.

5 mg: FD&C Blue no. 1 aluminum lake, FD&C Blue no. 2 aluminum lake, hypromellose, polyethylene glycol, talc and titanium dioxide.

The product meets USP Dissolution Test 2.

12 CLINICAL PHARMACOLOGY

12.1 Mechanism of Action

Ropinirole is a non-ergoline dopamine agonist. The precise mechanism of action of ropinirole as a treatment for Parkinson’s disease is unknown, although it is thought to be related to its ability to stimulate dopamine D2 receptors within the caudate-putamen in the brain. The precise mechanism of action of ropinirole as a treatment for RLS is unknown, although it is thought to be related to its ability to stimulate dopamine receptors.

12.2 Pharmacodynamics

Clinical experience with dopamine agonists, including ropinirole, suggests an association with impaired ability to regulate blood pressure resulting in orthostatic hypotension, especially during dose escalation. In some patients in clinical trials, blood pressure changes were associated with the emergence of orthostatic symptoms, bradycardia, and, in one case in a healthy volunteer, transient sinus arrest with syncope [see Warnings and Precautions (5.2, 5.3)].

The mechanism of orthostatic hypotension induced by ropinirole is presumed to be due to a D2-mediated blunting of the noradrenergic response to standing and subsequent decrease in peripheral vascular resistance. Nausea is a common concomitant symptom of orthostatic signs and symptoms.

At oral doses as low as 0.2 mg, ropinirole suppressed serum prolactin concentrations in healthy male volunteers.

Ropinirole had no dose-related effect on electrocardiogram wave form and rhythm in young, healthy, male volunteers in the range of 0.01 to 2.5 mg.

Ropinirole had no dose- or exposure-related effect on mean QT intervals in healthy male and female volunteers titrated to doses up to 4 mg/day. The effect of ropinirole on QTc intervals at higher exposures achieved either due to drug interactions, hepatic impairment, or at higher doses has not been systematically evaluated.

12.3 Pharmacokinetics

Ropinirole displayed linear kinetics over the dosing range of 1 to 8 mg 3 times daily. Steady-state concentrations are expected to be achieved within 2 days of dosing. Accumulation upon multiple dosing is predictive from single dosing.

Absorption

Ropinirole is rapidly absorbed after oral administration, reaching peak concentration in approximately 1 to 2 hours. In clinical trials, more than 88% of a radiolabeled dose was recovered in urine and the absolute bioavailability was 45% to 55%, indicating approximately 50% first-pass effect.

Relative bioavailability from a tablet compared with an oral solution is 85%. Food does not affect the extent of absorption of ropinirole, although its Tmax is increased by 2.5 hours and its Cmax is decreased by approximately 25% when the drug is taken with a high-fat meal.

Distribution

Ropinirole is widely distributed throughout the body, with an apparent volume of distribution of 7.5 L/kg. It is up to 40% bound to plasma proteins and has a blood-to-plasma ratio of 1:1.

Metabolism

Ropinirole is extensively metabolized by the liver. The major metabolic pathways are N-despropylation and hydroxylation to form the inactive N-despropyl metabolite and hydroxy metabolites. The N-despropyl metabolite is converted to carbamyl glucuronide, carboxylic acid, and N-despropyl hydroxy metabolites. The hydroxy metabolite of ropinirole is rapidly glucuronidated.

In vitro studies indicate that the major cytochrome P450 enzyme involved in the metabolism of ropinirole is CYP1A2, an enzyme known to be induced by smoking and omeprazole and inhibited by, for example, fluvoxamine, mexiletine, and the older fluoroquinolones such as ciprofloxacin and norfloxacin.

Elimination

The clearance of ropinirole after oral administration is 47 L/h and its elimination half-life is approximately 6 hours. Less than 10% of the administered dose is excreted as unchanged drug in urine. N-despropyl ropinirole is the predominant metabolite found in urine (40%), followed by the carboxylic acid metabolite (10%) and the glucuronide of the hydroxy metabolite (10%).

Specific Populations

Because therapy with ropinirole is initiated at a low dose and gradually titrated upward according to clinical tolerability to obtain the optimum therapeutic effect, adjustment of the initial dose based on gender, weight, or age is not necessary.

Geriatric Patients: Oral clearance of ropinirole is reduced by 15% in patients older than 65 years compared with younger patients. Dosage adjustment is not necessary in the elderly (older than 65 years), as the dose of ropinirole is to be individually titrated to clinical response.

Male and Female Patients: Male and female patients showed similar clearance.

Racial or Ethnic Groups: The influence of race on the pharmacokinetics of ropinirole has not been evaluated.

Cigarette Smoking: Smoking is expected to increase the clearance of ropinirole since CYP1A2 is known to be induced by smoking. In a trial in patients with RLS, smokers (n = 7) had an approximately 30% lower Cmax and a 38% lower AUC than did nonsmokers (n = 11) when those parameters were normalized for dose.

Patients with Renal Impairment: Based on population pharmacokinetic analysis, no difference was observed in the pharmacokinetics of ropinirole in subjects with moderate renal impairment (creatinine clearance between 30 to 50 mL/min) compared with an age-matched population with creatinine clearance above 50 mL/min. Therefore, no dosage adjustment is necessary in patients with moderate renal impairment.

A trial of ropinirole in subjects with end-stage renal disease on hemodialysis has shown that clearance of ropinirole was reduced by approximately 30%. The recommended maximum dose is lower in these patients [see Dosage and Administration (2.2, 2.3)].

The use of ropinirole in subjects with severe renal impairment (creatinine clearance <30 mL/min) without regular dialysis has not been studied.

Patients with Hepatic Impairment: The pharmacokinetics of ropinirole have not been studied in patients with hepatic impairment. Because ropinirole is extensively metabolized by the liver, these patients may have higher plasma levels and lower clearance of ropinirole than patients with normal hepatic function.

Other Diseases: Population pharmacokinetic analysis revealed no change in the clearance of ropinirole in patients with concomitant diseases such as hypertension, depression, osteoporosis/arthritis, and insomnia compared with patients with Parkinson’s disease only.

Drug Interaction Studies

Digoxin: Coadministration of ropinirole (2 mg 3 times daily) with digoxin (0.125 to 0.25 mg once daily) did not alter the steady-state pharmacokinetics of digoxin in 10 patients.

Theophylline: Administration of theophylline (300 mg twice daily), a substrate of CYP1A2, did not alter the steady-state pharmacokinetics of ropinirole (2 mg 3 times daily) in 12 patients with Parkinson’s disease. Ropinirole (2 mg 3 times daily) did not alter the pharmacokinetics of theophylline (5 mg/kg intravenously) in 12 patients with Parkinson’s disease.

Ciprofloxacin: Coadministration of ciprofloxacin (500 mg twice daily), an inhibitor of CYP1A2, with ropinirole (2 mg 3 times daily) increased ropinirole AUC by 84% on average and Cmax by 60% (n = 12 patients).

Estrogens: Population pharmacokinetic analysis revealed that estrogens (mainly ethinylestradiol: intake 0.6 to 3 mg over 4-month to 23-year period) reduced the oral clearance of ropinirole by 36% in 16 patients.

L-dopa: Coadministration of carbidopa + L-dopa (10/100 mg twice daily) with ropinirole (2 mg 3 times daily) had no effect on the steady-state pharmacokinetics of ropinirole (n = 28 patients). Oral administration of ropinirole 2 mg 3 times daily increased mean steady-state Cmax of L-dopa by 20%, but its AUC was unaffected (n = 23 patients).

Commonly Administered Drugs: Population analysis showed that commonly administered drugs (e.g., selegiline, amantadine, tricyclic antidepressants, benzodiazepines, ibuprofen, thiazides, antihistamines, anticholinergics) did not affect the clearance of ropinirole. An in vitro study indicates that ropinirole is not a substrate for P-glycoprotein. Ropinirole and its circulating metabolites do not inhibit or induce P450 enzymes; therefore, ropinirole is unlikely to affect the pharmacokinetics of other drugs by a P450 mechanism.

13 NONCLINICAL TOXICOLOGY

13.1 Carcinogenesis, Mutagenesis, Impairment of Fertility

Carcinogenesis

Two-year carcinogenicity studies of ropinirole were conducted in mice at oral doses of 0, 5, 15, and 50 mg/kg/day and in rats at oral doses of 0, 1.5, 15, and 50 mg/kg/day.

In rats, there was an increase in testicular Leydig cell adenomas at all doses tested. The lowest dose tested (1.5 mg/kg/day) is less than the MRHD for Parkinson’s disease (24 mg/day) on a mg/m^2 basis. The endocrine mechanisms believed to be involved in the production of these tumors in rats are not considered relevant to humans.

In mice, there was an increase in benign uterine endometrial polyps at a dose of 50 mg/kg/day. The highest dose not associated with this finding (15 mg/kg/day) is 3 times the MRHD on a mg/m^2 basis.

Mutagenesis

Ropinirole was not mutagenic or clastogenic in in vitro (Ames, chromosomal aberration in human lymphocytes, mouse lymphoma tk) assays, or in the in vivo mouse micronucleus test.

Impairment of Fertility

When administered to female rats prior to and during mating and throughout pregnancy, ropinirole caused disruption of implantation at oral doses of 20 mg/kg/day (8 times the MRHD on a mg/m^2 basis) or greater. This effect in rats is thought to be due to the prolactin-lowering effect of ropinirole. In rat studies using a low oral dose (5 mg/kg) during the prolactin-dependent phase of early pregnancy (gestation days 0 to 8), ropinirole did not affect female fertility at oral doses up to 100 mg/kg/day (40 times the MRHD on a mg/m^2 basis). No effect on male fertility was observed in rats at oral doses up to 125 mg/kg/day (50 times the MRHD on a mg/m^2 basis).

14 CLINICAL STUDIES

14.1 Parkinson's Disease

The effectiveness of ropinirole in the treatment of Parkinson’s disease was evaluated in a multinational drug development program consisting of 11 randomized, controlled trials. Four trials were conducted in patients with early Parkinson’s disease and no concomitant L-dopa and 7 trials were conducted in patients with advanced Parkinson’s disease with concomitant L-dopa.

Three placebo-controlled trials provide evidence of effectiveness of ropinirole in the management of patients with Parkinson’s disease who were and were not receiving concomitant L-dopa. Two of these 3 trials enrolled patients with early Parkinson’s disease (without L-dopa) and 1 enrolled patients receiving L-dopa.

In these trials a variety of measures were used to assess the effects of treatment (e.g., the Unified Parkinson’s Disease Rating Scale [UPDRS], Clinical Global Impression [CGI] scores, patient diaries recording time “on” and “off,” tolerability of L-dopa dose reductions).

In both trials of patients with early Parkinson’s disease (without L-dopa), the motor component (Part III) of the UPDRS was the primary outcome assessment. The UPDRS is a multi-item rating scale intended to evaluate mentation (Part I), activities of daily living (Part II), motor performance (Part III), and complications of therapy (Part IV). Part III of the UPDRS contains 14 items designed to assess the severity of the cardinal motor findings in patients with Parkinson’s disease (e.g., tremor, rigidity, bradykinesia, postural instability) scored for different body regions and has a maximum (worst) score of 108. In the trial of patients with advanced Parkinson’s disease (with L-dopa), both reduction in percent awake time spent “off” and the ability to reduce the daily use of L-dopa were assessed as a combined endpoint and individually.

Trials in Patients with Early Parkinson’s Disease (without L-dopa)

Trial 1 was a 12-week multicenter trial in which 63 patients with idiopathic Parkinson’s disease receiving concomitant anti-Parkinson medication (but not L-dopa) were enrolled and 41 were randomized to ropinirole and 22 to placebo. Patients had a mean disease duration of approximately 2 years. Patients were eligible for enrollment if they presented with bradykinesia and at least tremor, rigidity, or postural instability. In addition, they must have been classified as Hoehn & Yahr Stage I to IV. This scale, ranging from I = unilateral involvement with minimal impairment to V = confined to wheelchair or bed, is a standard instrument used for staging patients with Parkinson’s disease. The primary outcome measure in this trial was the proportion of patients experiencing a decrease (compared with baseline) of at least 30% in the UPDRS motor score.

Patients were titrated for up to 10 weeks, starting at 0.5 mg twice daily, with weekly increments of 0.5 mg twice daily to a maximum of 5 mg twice daily. Once patients reached their maximally tolerated dose (or 5 mg twice daily), they were maintained on that dose through 12 weeks. The mean dose achieved by patients at trial endpoint was 7.4 mg/day. Mean baseline UPDRS motor score was 18.6 for patients treated with ropinirole and 19.9 for patients treated with placebo. At the end of 12 weeks, the percentage of responders was greater on ropinirole than on placebo and the difference was statistically significant (Table 6).

Table 6. Percent Responders for Unified Parkinson’s Disease Rating Scale Motor Score in Trial 1 (Intent-to-Treat Population)

 | Responders | Difference from Placebo
Placebo | 41% | NA
Ropinirole | 71% | 30%

Trial 2 in patients with early Parkinson’s disease (without L-dopa) was a double-blind, randomized, placebo-controlled, 6-month trial. In this trial, 241 patients were enrolled and 116 were randomized to ropinirole and 125 to placebo. Patients were essentially similar to those in the trial described above; concomitant use of selegiline was allowed, but patients were not permitted to use anticholinergics or amantadine during the trial. Patients had a mean disease duration of 2 years and limited (not more than a 6-week period) or no prior exposure to L-dopa. The starting dosage of ropinirole in this trial was 0.25 mg 3 times daily. The dosage was titrated at weekly intervals by increments of 0.25 mg 3 times daily to a dosage of 1 mg 3 times daily. Further titrations at weekly intervals were at increments of 0.5 mg 3 times daily up to a dosage of 3 mg 3 times daily, and then weekly at increments of 1 mg 3 times daily. Patients were to be titrated to a dosage of at least 1.5 mg 3 times daily and then to their maximally tolerated dosage, up to a maximum of 8 mg 3 times daily. The mean dose attained in patients at trial endpoint was 15.7 mg/day.

The primary measure of effectiveness was the mean percent reduction (improvement) from baseline in the UPDRS motor score. At the end of the 6-month trial, patients treated with ropinirole showed improvement in motor score compared with placebo and the difference was statistically significant (Table 7).

Table 7. Mean Percentage Change from Baseline in Unified Parkinson’s Disease Rating Scale (UPDRS) Motor Score at End of Treatment in Trial 2 (Intent-to-Treat Population)

Treatment | Baseline UPDRS Motor Score | Mean Change from Baseline | Difference from Placebo
Placebo | 17.7 | +4% | NA
Ropinirole | 17.9 | -22% | -26%

Trial in Patients with Advanced Parkinson’s Disease (with L-dopa)

Trial 3 was a double-blind, randomized, placebo-controlled, 6-month trial that randomized 149 patients (Hoehn & Yahr II to IV) who were not adequately controlled on L-dopa. Ninety-five patients were randomized to ropinirole and 54 were randomized to placebo. Patients in this trial had a mean disease duration of approximately 9 years, had been exposed to L-dopa for approximately 7 years, and had experienced “on-off” periods with L-dopa therapy. Patients previously receiving stable doses of selegiline, amantadine, and/or anticholinergic agents could continue on these agents during the trial. Patients were started at a dosage of 0.25 mg 3 times daily of ropinirole and titrated upward by weekly intervals until an optimal therapeutic response was achieved. The maximum dosage of trial medication was 8 mg 3 times daily. All patients had to be titrated to at least a dosage of 2.5 mg 3 times daily. Patients could then be maintained on this dosage level or higher for the remainder of the trial. Once a dosage of 2.5 mg 3 times daily was achieved, patients underwent a mandatory reduction in their L-dopa dosage, to be followed by additional mandatory reductions with continued escalation of the dosage of ropinirole. Reductions in the dosage of L-dopa were also allowed if patients experienced adverse reactions that the investigator considered related to dopaminergic therapy. The mean dose attained at trial endpoint was 16.3 mg/day. The primary outcome was the proportion of responders, defined as patients who were able both to achieve a decrease (compared with baseline) of at least 20% in their L-dopa dosage and a decrease of at least 20% in the proportion of the time awake in the “off” condition (a period of time during the day when patients are particularly immobile), as determined by subject diary. In addition, the mean change in “off” time from baseline and the percent change from baseline in daily L-dopa dosage were examined.

At the end of 6 months, the percentage of responders was greater on ropinirole than on placebo and the difference was statistically significant (Table 8).

Based on the protocol-mandated reductions in L-dopa dosage with escalating doses of ropinirole, patients treated with ropinirole had a 19.4% mean reduction in L-dopa dosage while patients treated with placebo had a 3% reduction. Mean daily L-dopa dosage at baseline was 759 mg for patients treated with ropinirole and 843 mg for patients treated with placebo.

The mean number of daily “off” hours at baseline was 6.4 hours for patients treated with ropinirole and 7.3 hours for patients treated with placebo. At the end of the 6-month trial, there was a mean reduction of 1.5 hours of “off” time in patients treated with ropinirole and a mean reduction of 0.9 hours of “off” time in patients treated with placebo, resulting in a treatment difference of 0.6 hours of “off” time.

Table 8. Mean Responder Percentage of Patients Reducing Daily L-Dopa Dosage by at Least 20% and Daily Proportion of “Off” Time by at Least 20% at End of Treatment in Trial 3 (Intent-to-Treat Population)

Treatment | Responders | Difference from Placebo
Placebo | 11% | NA
Ropinirole | 28% | 17%

14.2 Restless Legs Syndrome

The effectiveness of ropinirole in the treatment of RLS was demonstrated in randomized, double-blind, placebo-controlled trials in adults diagnosed with RLS using the International Restless Legs Syndrome Study Group diagnostic criteria. Patients were required to have a history of a minimum of 15 RLS episodes/month during the previous month and a total score of ≥15 on the International RLS Rating Scale (IRLS scale) at baseline. Patients with RLS secondary to other conditions (e.g., pregnancy, renal failure, anemia) were excluded. All trials employed flexible dosing, with patients initiating therapy at 0.25 mg ropinirole once daily. Patients were titrated based on clinical response and tolerability over 7 weeks to a maximum of 4 mg once daily. All doses were taken between 1 and 3 hours before bedtime.

A variety of measures were used to assess the effects of treatment, including the IRLS scale and Clinical Global Impression-Global Improvement (CGI-I) scores. The IRLS scale contains 10 items designed to assess the severity of sensory and motor symptoms, sleep disturbance, daytime somnolence, and impact on activities of daily living and mood associated with RLS. The range of scores is 0 to 40, with 0 being absence of RLS symptoms and 40 the most severe symptoms. Three of the controlled trials utilized the change from baseline in the IRLS scale at the Week 12 endpoint as the primary efficacy outcome.

Three hundred eighty patients were randomized to receive ropinirole (n = 187) or placebo (n = 193) in a U.S. trial (RLS-1); 284 were randomized to receive either ropinirole (n = 146) or placebo (n = 138) in a multinational trial (excluding U.S.) (RLS-2); and 267 patients were randomized to ropinirole (n = 131) or placebo (n = 136) in a multinational trial (including U.S.) (RLS-3). Across the 3 trials, the mean duration of RLS was 16 to 22 years (range: 0 to 65 years), mean age was approximately 54 years (range: 18 to 79 years), and approximately 61% were women. The mean dose at Week 12 was approximately 2 mg/day for the 3 trials.

At baseline, mean total IRLS score was 22 for ropinirole and 21.6 for placebo in RLS-1, 24.4 for ropinirole and 25.2 for placebo in RLS-2, and 23.6 for ropinirole and 24.8 for placebo in RLS-3. In all 3 trials, a statistically significant difference between the treatment group receiving ropinirole and the treatment group receiving placebo was observed at Week 12 for both the mean change from baseline in the IRLS scale total score and the percentage of patients rated as responders (much improved or very much improved) on the CGI-I (see Table 9).

Table 9. Mean Change in Total IRLS Rating Scale Score and Percent Responders on CGI-I

 | Ropinirole | Placebo | Difference from Placebo
Mean change in total IRLS scale score at Week 12
RLS-1 | -13.5 | -9.8 | -3.7
RLS-2 | -11 | -8 | -3
RLS-3 | -11.2 | -8.7 | -2.5
Percent responders on CGI-I at Week 12
RLS-1 | 73.3% | 56.5% | 16.8%
RLS-2 | 53.4% | 40.9% | 12.5%
RLS-3 | 59.5% | 39.6% | 19.9%

IRLS = International Restless Legs Syndrome, CGI-I = Clinical Global Impression-Global Improvement, RLS = Restless Legs Syndrome.

Long-term maintenance of efficacy in the treatment of RLS was demonstrated in a 36-week trial. Following a 24-week, single-blind treatment phase (flexible dosages of ropinirole of 0.25 to 4 mg once daily), patients who were responders (defined as a decrease of >6 points on the IRLS scale total score relative to baseline) were randomized in double-blind fashion to placebo or continuation of ropinirole for an additional 12 weeks. Relapse was defined as an increase of at least 6 points on the IRLS scale total score to a total score of at least 15, or withdrawal due to lack of efficacy. For patients who were responders at Week 24, the mean dose of ropinirole was 2 mg (range: 0.25 to 4 mg). Patients continued on ropinirole demonstrated a significantly lower relapse rate compared with patients randomized to placebo (32.6% versus 57.8%, P = 0.0156).

16 HOW SUPPLIED/STORAGE AND HANDLING

Product: 50090-1822

NDC: 50090-1822-0 100 TABLET, FILM COATED in a BOTTLE

Product: 50090-2068

17 PATIENT COUNSELING INFORMATION

Advise the patient to read the FDA-approved patient labeling (Patient Information).

Dosing Instructions

Instruct patients to take ropinirole tablets only as prescribed. If a dose is missed, advise patients not to double their next dose. Ropinirole tablets can be taken with or without food [see Dosage and Administration (2.1)].

Ropinirole is the active ingredient in ropinirole tablets (the immediate-release formulation). Ask your patients if they are taking another medication containing ropinirole.

Hypersensitivity/Allergic Reactions

Advise patients about the potential for developing a hypersensitivity/allergic reaction including manifestations such as urticaria, angioedema, rash, and pruritus when taking any ropinirole product. Inform patients who experience these or similar reactions to immediately contact their healthcare professional [see Contraindications (4)].

Falling Asleep during Activities of Daily Living and Somnolence

Alert patients to the potential sedating effects caused by ropinirole tablets, including somnolence and the possibility of falling asleep while engaged in activities of daily living. Because somnolence is a frequent adverse reaction with potentially serious consequences, patients should not drive a car, operate machinery, or engage in other potentially dangerous activities until they have gained sufficient experience with ropinirole tablets to gauge whether or not it adversely affects their mental and/or motor performance. Advise patients that if increased somnolence or episodes of falling asleep during activities of daily living (e.g., conversations, eating, driving a motor vehicle) are experienced at any time during treatment, they should not drive or participate in potentially dangerous activities until they have contacted their physician.

Advise patients of possible additive effects when patients are taking other sedating medications, alcohol, or other central nervous system depressants (e.g., benzodiazepines, antipsychotics, antidepressants) in combination with ropinirole tablets or when taking a concomitant medication (e.g., ciprofloxacin) that increases plasma levels of ropinirole [see Warnings and Precautions (5.1)].

Syncope and Hypotension/Orthostatic Hypotension

Advise patients that they may experience syncope and may develop hypotension with or without symptoms such as dizziness, nausea, syncope, and sometimes sweating while taking ropinirole tablets, especially if they are elderly. Hypotension and/or orthostatic symptoms may occur more frequently during initial therapy or with an increase in dose at any time (cases have been seen after weeks of treatment). Postural/orthostatic symptoms may be related to sitting up or standing. Accordingly, caution patients against standing rapidly after sitting or lying down, especially if they have been doing so for prolonged periods and especially at the initiation of treatment with ropinirole tablets [see Warnings and Precautions (5.2, 5.3)].

Hallucinations/Psychotic-Like Behavior

Inform patients that they may experience hallucinations (unreal visions, sounds, or sensations), and that other psychotic-like behavior can occur while taking ropinirole tablets. In patients with Parkinson’s disease, the elderly are at greater risk than younger patients. This risk is greater in patients who are taking ropinirole tablets with L-dopa or taking higher doses of ropinirole tablets and may also be further increased in patients taking any other drugs that increase dopaminergic tone. Tell patients to report hallucinations or psychotic-like behavior to their healthcare provider promptly should they develop [see Warnings and Precautions (5.4)].

Dyskinesia

Inform patients that ropinirole tablets may cause and/or exacerbate pre-existing dyskinesias [see Warnings and Precautions (5.5)].

Impulse Control/Compulsive Behaviors

Advise patients that they may experience impulse control and/or compulsive behaviors while taking ropinirole tablets. Advise patients to inform their physician or healthcare provider if they develop new or increased gambling urges, sexual urges, uncontrolled spending, binge or compulsive eating, or other urges while being treated with ropinirole tablets. Physicians should consider dose reduction or stopping the medication if a patient develops such urges while taking ropinirole tablets [see Warnings and Precautions (5.6)].

Withdrawal-Emergent Hyperpyrexia and Confusion

Advise patients to contact their healthcare provider if they wish to discontinue ropinirole tablets or decrease the dose of ropinirole tablets. Advise patients who have been prescribed a lower dose or who have been withdrawn from the drug to notify their healthcare provider if they present with fever, muscular rigidity, or altered consciousness [see Warnings and Precautions (5.7)].

Withdrawal Symptoms

Advise patients that withdrawal symptoms may occur during or after discontinuation or dose reduction of ropinirole tablets. Advise patients who have been prescribed a lower dose or who have been withdrawn from the drug to notify their healthcare provider if they have withdrawal symptoms such as apathy, anxiety, depression, fatigue, insomnia, sweating, or pain. Notify patients that in case of severe withdrawal symptoms, a trial re-administration of a dopamine agonist at the lowest effective dose may be considered [see Warnings and Precautions (5.8)].

Augmentation and Rebound

Inform patients with RLS that augmentation and/or rebound may occur after starting treatment with ropinirole tablets [see Warnings and Precautions (5.9)].

Nursing Mothers

Because of the possibility that ropinirole may be excreted in breast milk, discuss the developmental and health benefits of breastfeeding along with the mother’s clinical need for ropinirole and any potential adverse effects on the breastfed child from ropinirole or from the underlying maternal condition [see Use in Specific Populations (8.2)]. Advise patients that ropinirole could inhibit lactation because ropinirole inhibits prolactin secretion.

Pregnancy

Because experience with ropinirole in pregnant women is limited and ropinirole has been shown to have adverse effects on embryofetal development in animals, including teratogenic effects, advise patients of this potential risk. Advise patients to notify their physician if they become pregnant or intend to become pregnant during therapy [see Use in Specific Populations (8.1)].

Distributed by:

Glenmark Pharmaceuticals Inc., USA
Elmwood Park, NJ 07407

Questions? 1 (888) 721-7115
www.glenmarkpharma-us.com

August 2025

PATIENT INFORMATION

rOPINIRole Tablets
(roe-PIN-i-ROLE)

If you have Parkinson’s disease, read this side.

If you have Restless Legs Syndrome (RLS), read the other side.

Important Note: Ropinirole extended-release tablets have not been studied in RLS and are not approved for the treatment of RLS. However, an immediate-release form of ropinirole is approved for the treatment of moderate to severe primary RLS (see other side of this leaflet).

What is the most important information I should know about ropinirole tablets?

Ropinirole tablets can cause serious side effects, including:

- Falling asleep during normal activities. You may fall asleep while doing normal activities such as driving a car, doing physical tasks, or using hazardous machinery while taking ropinirole tablets. You may suddenly fall asleep without being drowsy or without warning. This may result in having accidents. Your chances of falling asleep while doing normal activities while taking ropinirole tablets are greater if you take other medicines that cause drowsiness. Tell your healthcare provider right away if this happens. Before starting ropinirole tablets, be sure to tell your healthcare provider if you take any medicines that make you drowsy.
- Fainting. Fainting can happen, and sometimes your heart rate may be decreased. This can happen especially when you start taking ropinirole tablets or your dose is increased. Tell your healthcare provider if you faint, feel dizzy, or feel light-headed.
- Decrease in blood pressure. Ropinirole tablets can decrease your blood pressure (hypotension), especially when you start taking ropinirole tablets or when your dose is changed. If you faint or feel dizzy, nauseated, or sweaty when you stand up from sitting or lying down (orthostatic hypotension), this may mean that your blood pressure is decreased. When you change position from lying down or sitting to standing up, you should do it carefully and slowly. Call your healthcare provider if you have any of the symptoms of decreased blood pressure listed above.
- Increase in blood pressure. Ropinirole extended-release tablets may increase your blood pressure.
- Changes in heart rate (decrease or increase). Ropinirole tablets can decrease or increase your heart rate.
- Hallucinations and other psychotic-like behavior. Ropinirole tablets can cause or worsen psychotic-like behavior including hallucinations (seeing or hearing things that are not real), confusion, excessive suspicion, aggressive behavior, agitation, delusional beliefs (believing things that are not real), and disorganized thinking. The chances of having hallucinations or these other psychotic-like changes are higher in people with Parkinson’s disease who are taking ropinirole tablets or taking higher doses of these drugs. If you have hallucinations or any of these other psychotic-like changes, talk with your healthcare provider.
- Uncontrolled sudden movements. Ropinirole tablets may cause uncontrolled sudden movements or make such movements you already have worse or more frequent. Tell your healthcare provider if this happens. The doses of your anti-Parkinson’s medicine may need to be changed.
- Unusual urges. Some patients taking ropinirole tablets get urges to behave in a way unusual for them. Examples of this are an unusual urge to gamble, increased sexual urges and behaviors, or an uncontrollable urge to shop, spend money, or eat. If you notice or your family notices that you are developing any unusual behaviors, talk to your healthcare provider.
- Withdrawal Symptoms. Ropinirole tablets are dopamine agonist medicines. Dopamine agonist medicines, including ropinirole tablets can cause withdrawal symptoms as your dose is slowly lowered (tapered) or when treatment with ropinirole tablets is stopped. Tell your doctor right away if you get any of the following withdrawal symptoms:

- fever

- fatigue

- confusion

- sweating

- severe muscle stiffness

- pain

- insomnia

- feeling like you do not care about things you usually care about (apathy)

- depression

- anxiety

After you have stopped taking ropinirole tablets, your healthcare provider may need to restart you at a low dose of ropinirole tablets if you get severe withdrawal symptoms.

What are ropinirole tablets?

- Ropinirole tablets are short-acting prescription medicine containing ropinirole (usually taken 3 times a day) that is used to treat Parkinson’s disease. It is also used to treat a condition called Restless Legs Syndrome (RLS).
- Ropinirole extended-release tablets are a long-acting prescription medicine containing ropinirole (taken 1 time a day) that is used only to treat Parkinson’s disease but not to treat RLS.

Having one of these conditions does not mean you have or will develop the other condition.

You should not be taking more than 1 medicine containing ropinirole. Tell your healthcare provider if you are taking any other medicine containing ropinirole.

It is not known if ropinirole tablets are safe and effective for use in children younger than 18 years of age.

Do not take ropinirole tablets if you:

- are allergic to ropinirole or any of the ingredients in ropinirole tablets. See the end of this page for a complete list of the ingredients in ropinirole tablets.
- Get help right away if any of the symptoms of an allergic reaction cause problems swallowing or breathing. Call your healthcare provider if you have any of the symptoms of an allergic reaction. Symptoms of an allergic reaction may include:

- hives

- rash

- swelling of the face, lips, mouth, tongue, or throat

- itching

Before taking ropinirole tablets, tell your healthcare provider about all of your medical conditions, including if you:

- have daytime sleepiness from a sleep disorder or have unexpected or unpredictable sleepiness or periods of sleep.
- start or stop taking other medicines while you are taking ropinirole tablets. This may increase your chances of getting side effects.
- start or stop smoking while you are taking ropinirole tablets. Smoking may decrease the treatment effect of ropinirole tablets.
- feel dizzy, nauseated, sweaty, or faint when you stand up from sitting or lying down.
- drink alcoholic beverages. This may increase your chances of becoming drowsy or sleepy while taking ropinirole tablets.
- have high or low blood pressure.
- have or have had heart problems.
- are pregnant or plan to become pregnant. It is not known if ropinirole tablets can harm your unborn baby.
- are breastfeeding or plan to breastfeed. It is not known if ropinirole tablets passes into your breast milk. The amount of breast milk you make may be decreased while taking ropinirole tablets. Talk to your healthcare provider to decide if you should breastfeed while taking ropinirole tablets.

Tell your healthcare provider about all the medicines you take, including prescription and over-the-counter medicines, vitamins, and herbal supplements. Some of these medicines may increase your chances of getting side effects while taking ropinirole tablets.

How should I take ropinirole tablets?

- Take ropinirole tablets exactly as directed by your healthcare provider.
- Take ropinirole tablets with or without food.
- Do not suddenly stop taking ropinirole tablets without talking to your healthcare provider. If you stop this medicine, you may develop withdrawal symptoms (see “What is the most important information I should know about ropinirole tablets?”).
- Before starting ropinirole tablets, you should talk to your healthcare provider about what to do if you miss a dose. If you have missed the previous dose and it is time for your next dose, do not double the dose.
- Your healthcare provider will start you on a low dose of ropinirole tablets. Your healthcare provider will change the dose until you are taking the right amount of medicine to control your symptoms. It may take several weeks before you reach a dose that controls your symptoms.
- Contact your healthcare provider if you stop taking ropinirole tablets for any reason. Do not restart without talking with your healthcare provider.
- Your healthcare provider may prescribe ropinirole tablets alone, or add ropinirole tablets to medicine that you are already taking for Parkinson’s disease.
- You should not substitute ropinirole tablets for ropinirole extended release tablets, or ropinirole extended release tablets for ropinirole tablets without talking with your healthcare provider.

If you are taking ropinirole tablets:

- Ropinirole tablets are usually taken 3 times a day for Parkinson’s disease.

What are the possible side effects of ropinirole tablets?

Ropinirole tablets can cause serious side effects, including:

- See “What is the most important information I should know about ropinirole tablets?”

The most common side effects of ropinirole tablets include:

- fainting

- sleepiness or drowsiness

- hallucinations (seeing or hearing things that are not real)

- dizziness

- nausea or vomiting

- uncontrolled sudden movements

- upset stomach, abdominal pain or discomfort

- fatigue, tiredness, or weakness

- confusion

- headache

- leg swelling

- increased sweating

- constipation

- suddenly falling asleep

- high blood pressure (hypertension)

Tell your healthcare provider about any side effect that bothers you or that does not go away.

These are not all of the possible side effects with ropinirole tablets. Call your doctor for medical advice about side effects. You may report side effects to FDA at 1-800-FDA-1088.

How should I store ropinirole tablets?

- Store ropinirole tablets at room temperature between 68°F and 77°F (20°C and 25°C).
- Keep ropinirole tablets in a tightly closed container and out of direct sunlight.

Keep ropinirole tablets and all medicines out of the reach of children.

General information about the safe and effective use of ropinirole tablets:

Medicines are sometimes prescribed for purposes other than those listed in a Patient Information leaflet. Do not use ropinirole tablets for a condition for which it was not prescribed. Do not give ropinirole tablets to other people, even if they have the same symptoms that you have. It may harm them. You can ask your pharmacist or healthcare provider for information about ropinirole tablets that is written for health professionals.

What are the ingredients in ropinirole tablets?

The following ingredients are in ropinirole tablets:

Active ingredient: ropinirole (as ropinirole hydrochloride)

Inactive ingredients: citric acid anhydrous powder, croscarmellose sodium, lactose anhydrous, lactose monohydrate, magnesium stearate, microcrystalline cellulose. The ingredients of the film coating for each tablet are as follows:

0.25 mg: Hypromellose, polyethylene glycol, talc and titanium dioxide.

0.5 mg: FD&C Blue no. 2 aluminum lake, ferric oxide red, ferric oxide yellow, hypromellose, polyethylene glycol, talc and titanium dioxide.

1 mg: FD&C Blue no. 2 aluminum lake, ferric oxide black, ferric oxide yellow, hypromellose, polyethylene glycol, talc and titanium dioxide.

2 mg: Ferric oxide red, hypromellose, polyethylene glycol, talc and titanium dioxide.

3 mg: Carmine, FD&C Blue no. 2 aluminum lake, FD&C Yellow no. 6 aluminum lake, hypromellose, polyethylene glycol, talc and titanium dioxide.

4 mg: Ferric oxide black, ferric oxide red, ferric oxide yellow, hypromellose, polyethylene glycol, talc and titanium dioxide.

5 mg: FD&C Blue no. 1 aluminum lake, FD&C Blue no. 2 aluminum lake, hypromellose, polyethylene glycol, talc and titanium dioxide.

Distributed by:

Glenmark Pharmaceuticals Inc., USA
Elmwood Park, NJ 07407

Questions? 1 (888) 721-7115
www.glenmarkpharma-us.com

This Patient Information has been approved by the U.S. Food and Drug Administration.

August 2025

PATIENT INFORMATION

rOPINIRole Tablets
(roe-PIN-i-ROLE)

If you have Restless Legs Syndrome (RLS), read this side.

If you have Parkinson’s disease, read the other side.

Important Note: Ropinirole extended-release tablets have not been studied in RLS and is not approved for the treatment of RLS.

People with RLS should take ropinirole tablets differently than people with Parkinson’s disease (see “How should I take ropinirole tablets for RLS?” for the recommended dosing for RLS). A lower dose of ropinirole tablets is generally needed for people with RLS, and is taken once daily before bedtime.

What is the most important information I should know about ropinirole tablets?

Ropinirole tablets can cause serious side effects, including:

- Falling asleep during normal activities. You may fall asleep while doing normal activities such as driving a car, doing physical tasks, or using hazardous machinery while taking ropinirole tablets. You may suddenly fall asleep without being drowsy or without warning. This may result in having accidents. Your chances of falling asleep while doing normal activities while taking ropinirole tablets are greater if you take other medicines that cause drowsiness. Tell your healthcare provider right away if this happens. Before starting ropinirole tablets, be sure to tell your healthcare provider if you take any medicines that make you drowsy.
- Fainting. Fainting can happen, and sometimes your heart rate may be decreased. This can happen especially when you start taking ropinirole tablets or your dose is increased. Tell your healthcare provider if you faint, feel dizzy, or feel light-headed.
- Decrease in blood pressure. Ropinirole tablets can decrease your blood pressure (hypotension), especially when you start taking ropinirole tablets or when your dose is changed. If you faint or feel dizzy, nauseated, or sweaty when you stand up from sitting or lying down (orthostatic hypotension), this may mean that your blood pressure is decreased. When you change position from lying down or sitting to standing up, you should do it carefully and slowly. Call your healthcare provider if you have any of the symptoms of decreased blood pressure listed above.
- Hallucinations and other psychotic-like behavior. Ropinirole tablets can cause or worsen psychotic-like behavior including hallucinations (seeing or hearing things that are not real), confusion, excessive suspicion, aggressive behavior, agitation, delusional beliefs (believing things that are not real), and disorganized thinking. If you have hallucinations or any of these other psychotic-like changes, talk with your healthcare provider.
- Unusual urges. Some patients taking ropinirole tablets get urges to behave in a way unusual for them. Examples of this are an unusual urge to gamble, increased sexual urges and behaviors, or an uncontrollable urge to shop, spend money, or eat. If you notice or your family notices that you are developing any unusual behaviors, talk to your healthcare provider.
- Withdrawal Symptoms. Ropinirole tablets are a dopamine agonist medicine. Dopamine agonist medicines, including ropinirole tablets, can cause withdrawal symptoms as your dose is slowly lowered (tapered) or when treatment with ropinirole tablets is stopped. Tell your doctor right away if you get any of the following withdrawal symptoms:

- fever

- fatigue

- confusion

- sweating

- severe muscle stiffness

- pain

- insomnia

- feeling like you do not care about things you usually care about (apathy)

- depression

- anxiety

After you have stopped taking ropinirole tablets, your healthcare provider may need to restart you at a low dose of ropinirole tablets if you get severe withdrawal symptoms.

- Changes in RLS symptoms. Ropinirole tablets may cause RLS to come back in the morning (rebound), happen earlier in the evening, or even happen in the afternoon.

What are ropinirole tablets?

Ropinirole tablets are a prescription medicine containing ropinirole used to treat moderate-to-severe primary RLS. It is also used to treat Parkinson’s disease.

Having one of these conditions does not mean you have or will develop the other condition.

You should not be taking more than 1 medicine containing ropinirole. Tell your healthcare provider if you are taking any other medicine containing ropinirole.

It is not known if ropinirole tablets are safe and effective for use in children younger than 18 years of age.

Do not take ropinirole tablets if you:

- are allergic to ropinirole or any of the ingredients in ropinirole tablets. See the end of this page for a complete list of the ingredients in ropinirole tablets.
- Get help right away if any of the symptoms of an allergic reaction cause problems swallowing or breathing. Call your healthcare provider if you have any of the symptoms of an allergic reaction. Symptoms of an allergic reaction may include:

- hives

- rash

- swelling of the face, lips, mouth, tongue, or throat

- itching

Before taking ropinirole tablets, tell your healthcare provider about all of your medical conditions, including if you:

- have daytime sleepiness from a sleep disorder or have unexpected or unpredictable sleepiness or periods of sleep.
- start or stop taking other medicines while you are taking ropinirole tablets. This may increase your chances of getting side effects.
- start or stop smoking while you are taking ropinirole tablets. Smoking may decrease the treatment effect of ropinirole tablets.
- feel dizzy, nauseated, sweaty, or faint when you stand up from sitting or lying down.
- drink alcoholic beverages. This may increase your chances of becoming drowsy or sleepy while taking ropinirole tablets.
- have high or low blood pressure.
- have or have had heart problems.
- are pregnant or plan to become pregnant. It is not known if ropinirole tablets can harm your unborn baby.
- are breastfeeding or plan to breastfeed. It is not known if ropinirole tablets passes into your breast milk. The amount of breast milk you make may be decreased while taking ropinirole tablets. Talk to your healthcare provider to decide if you should breastfeed while taking ropinirole tablets.

Tell your healthcare provider about all the medicines you take, including prescription and over-the-counter medicines, vitamins, and herbal supplements. Some of these medicines may increase your chances of getting side effects while taking ropinirole tablets.

How should I take ropinirole tablets?

- Take ropinirole tablets exactly as directed by your healthcare provider.
- Ropinirole tablets are usually taken once in the evening, 1 to 3 hours before bedtime.
- Take ropinirole tablets with or without food.
- Do not suddenly stop taking ropinirole tablets without talking to your healthcare provider. If you stop this medicine, you may develop withdrawal symptoms (see “What is the most important information I should know about ropinirole tablets?”).
- Your healthcare provider will start you on a low dose of ropinirole tablets. Your healthcare provider may change the dose until you are taking the right amount of medicine to control your symptoms.
- If you miss your dose, do not double your next dose. Take only your usual dose 1 to 3 hours before your next bedtime.
- Contact your healthcare provider if you stop taking ropinirole tablets for any reason. Do not restart without talking with your healthcare provider.

What are the possible side effects of ropinirole tablets?

Ropinirole tablets can cause serious side effects, including:

- See “What is the most important information I should know about ropinirole tablets?”

The most common side effects of ropinirole tablets include:

- nausea or vomiting

- drowsiness or sleepiness

- dizziness

- fatigue, tiredness, or weakness

Tell your healthcare provider about any side effect that bothers you or that does not go away.

These are not all of the possible side effects with ropinirole tablets. Call your doctor for medical advice about side effects. You may report side effects to FDA at 1-800-FDA-1088.

How should I store ropinirole tablets?

- Store ropinirole tablets at room temperature between 68°F and 77°F (20°C and 25°C).
- Keep ropinirole tablets in a tightly closed container and out of direct sunlight.

Keep ropinirole tablets and all medicines out of the reach of children.

General information about the safe and effective use of ropinirole tablets:

Medicines are sometimes prescribed for purposes other than those listed in a Patient Information leaflet. Do not use ropinirole tablets for a condition for which it was not prescribed. Do not give ropinirole tablets to other people, even if they have the same symptoms that you have. It may harm them. You can ask your pharmacist or healthcare provider for information about ropinirole tablets that is written for health professionals.

What are the ingredients in ropinirole tablets?

Active ingredient: ropinirole (as ropinirole hydrochloride)

Inactive ingredients: citric acid anhydrous powder, croscarmellose sodium, lactose anhydrous, lactose monohydrate, magnesium stearate, microcrystalline cellulose. The ingredients of the film coating for each tablet are as follows:

0.25 mg: Hypromellose, polyethylene glycol, talc and titanium dioxide.

0.5 mg: FD&C Blue no. 2 aluminum lake, ferric oxide red, ferric oxide yellow, hypromellose, polyethylene glycol, talc and titanium dioxide.

1 mg: FD&C Blue no. 2 aluminum lake, ferric oxide black, ferric oxide yellow, hypromellose, polyethylene glycol, talc and titanium dioxide.

2 mg: Ferric oxide red, hypromellose, polyethylene glycol, talc and titanium dioxide.

3 mg: Carmine, FD&C Blue no. 2 aluminum lake, FD&C Yellow no. 6 aluminum lake, hypromellose, polyethylene glycol, talc and titanium dioxide.

4 mg: Ferric oxide black, ferric oxide red, ferric oxide yellow, hypromellose, polyethylene glycol, talc and titanium dioxide.

5 mg: FD&C Blue no. 1 aluminum lake, FD&C Blue no. 2 aluminum lake, hypromellose, polyethylene glycol, talc and titanium dioxide.

Distributed by:

Glenmark Pharmaceuticals Inc., USA
Elmwood Park, NJ 07407

Questions? 1 (888) 721-7115
www.glenmarkpharma-us.com

This Patient Information has been approved by the U.S. Food and Drug Administration.

August 2025